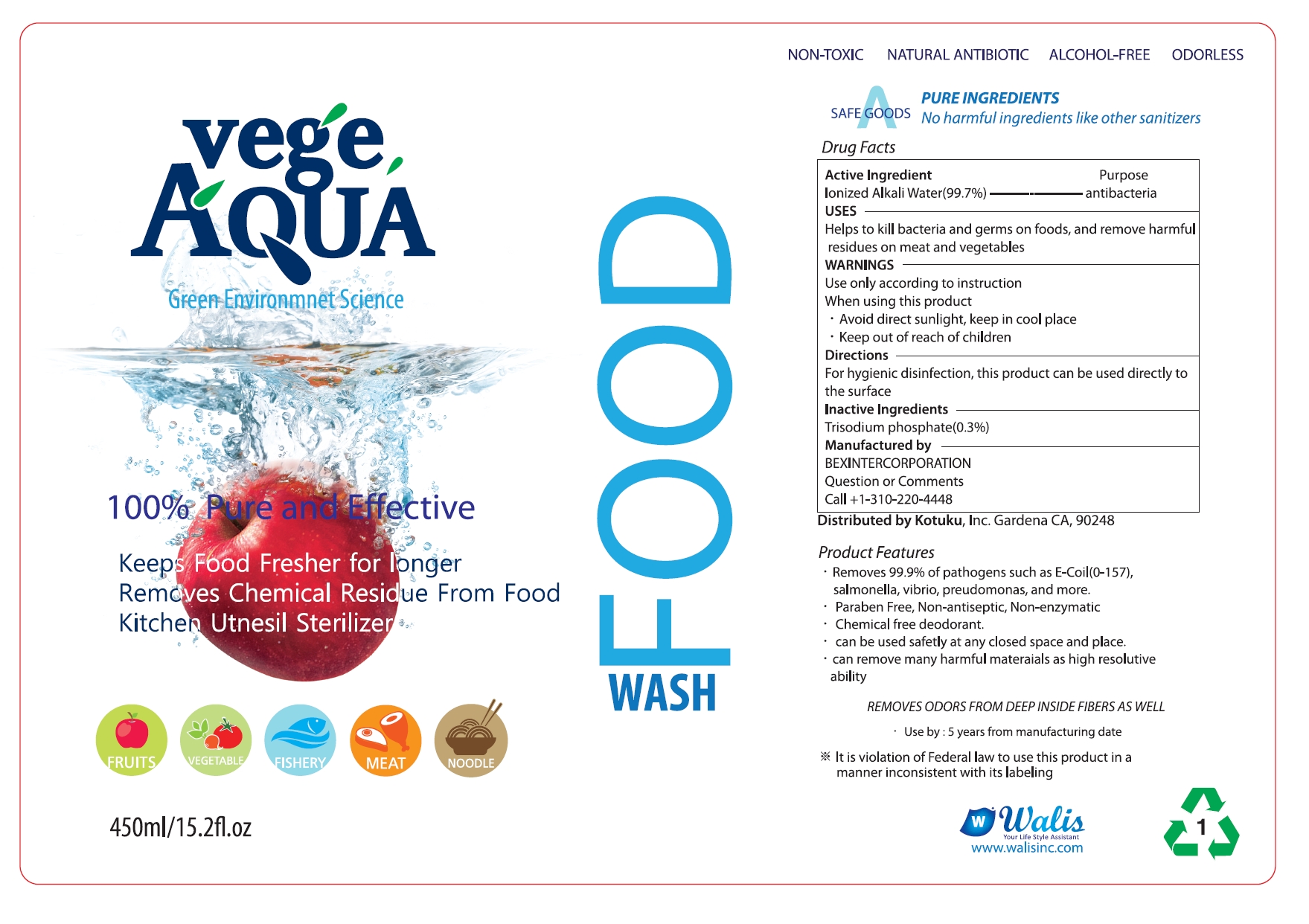 DRUG LABEL: VEGE AQUA
NDC: 72515-101 | Form: LIQUID
Manufacturer: WALIS, INC.
Category: otc | Type: HUMAN OTC DRUG LABEL
Date: 20190218

ACTIVE INGREDIENTS: SODIUM PHOSPHATE, TRIBASIC, DODECAHYDRATE 1.425 g/475 mL
INACTIVE INGREDIENTS: WATER

VEGE AQUA